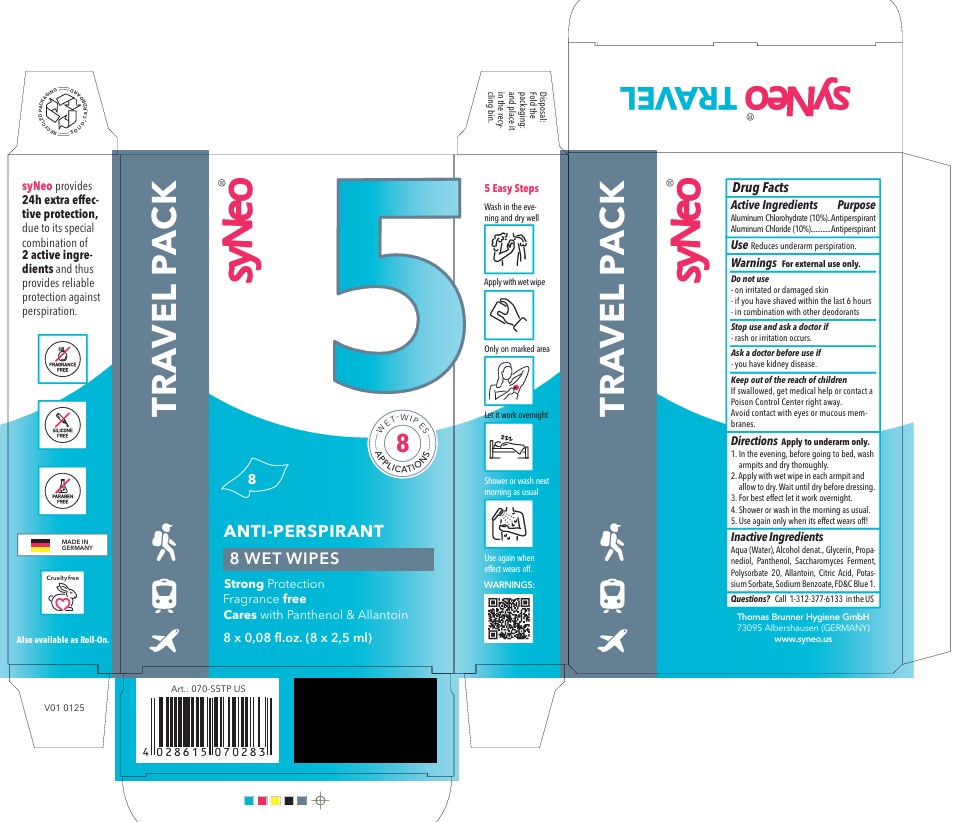 DRUG LABEL: SyNeo ANTI PERSPIRANT
NDC: 85118-004 | Form: CELLULAR SHEET
Manufacturer: Thomas Brunner Hygiene GmbH
Category: otc | Type: HUMAN OTC DRUG LABEL
Date: 20250221

ACTIVE INGREDIENTS: ALUMINUM CHLOROHYDRATE 10 g/100 mL; ALUMINUM CHLORIDE 10 g/100 mL
INACTIVE INGREDIENTS: WATER; GLYCERIN; PANTHENOL; PATENT BLUE V; ALCOHOL; PROPANEDIOL; POLYSORBATE 20; SACCHAROMYCES LYSATE; ALLANTOIN

SyNeo ANTI-PERSPIRANT 8 WET WIPES

Drug Facts

ACTIVE INGREDIENT

Active Ingredients | Purpose
Aluminum Chlorohydrate (10%) | Antiperspirant
Aluminum Chloride (10%) | Antiperspirant

Use

Reduces underarm perspiration.

Warnings

For external use only.

Do not use

- on irritated or damaged skin
- if you have shaved within the last 6 hours
- in combination with other deodorants

Stop use and ask a doctor if

- rash or irritation occurs.

Keep out of the reach of children

If swallowed, get medical help or contact a Poison Control Center right away.

Avoid contact with eyes or mucous membranes.

Directions

Apply to underarm only.

1. In the evening, before going to bed, wash armpits and dry thoroughly.
2. Apply with wet wipe in each armpit and allow to dry. Wait until dry before dressing.
3. For best effect let it work overnight.
4. Shower or wash in the morning as usual.
5. Use again only when its effect wears off!

Inactive Ingredients

Aqua (Water), Alcohol denat., Glycerin, Propanediol, Panthenol, Saccharomyces Ferment, Polysorbate 20, Allantoin, Citric Acid, Potassium Sorbate, Sodium Benzoate, FD&C Blue 1.

Questions?

Questions? Call 1-312-377-6133 in the US

SyNeo ANTI-PERSPIRANT 8 WET WIPES

SyNeo

WET-WIPES 8 APPLICATIONS

ANTI-PERSPIRANT

8 WET WIPES

Strong Protection

Fragrance free

Cares with Panthenol & Allantoin

8 x 0.08 fl.oz. (8 x 2.5 ml)